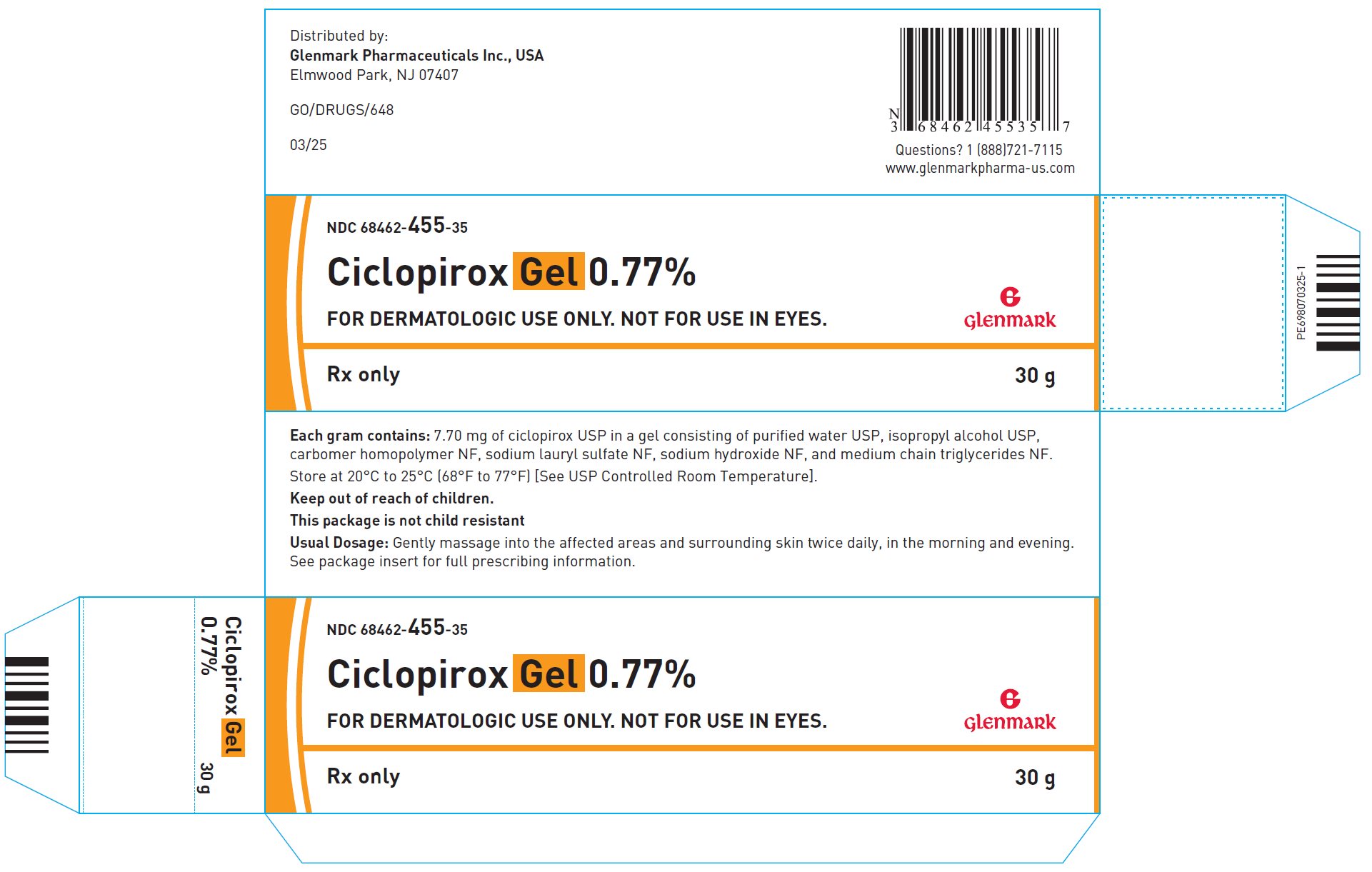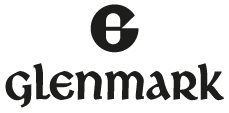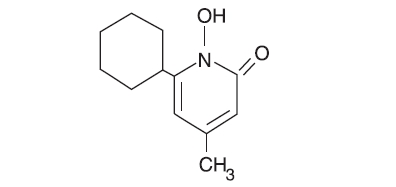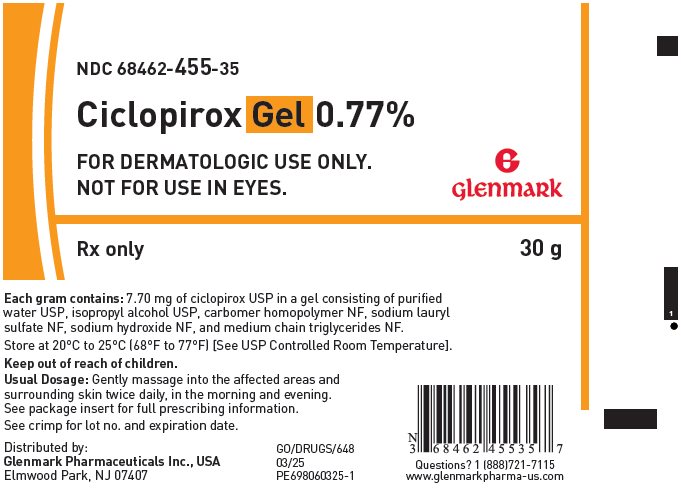 DRUG LABEL: ciclopirox
NDC: 68462-455 | Form: GEL
Manufacturer: Glenmark Pharmaceuticals Inc., USA
Category: prescription | Type: HUMAN PRESCRIPTION DRUG LABEL
Date: 20260123

ACTIVE INGREDIENTS: CICLOPIROX 7.7 mg/1 g
INACTIVE INGREDIENTS: CARBOMER HOMOPOLYMER TYPE C (ALLYL PENTAERYTHRITOL CROSSLINKED); ISOPROPYL ALCOHOL; MEDIUM-CHAIN TRIGLYCERIDES; SODIUM HYDROXIDE; SODIUM LAURYL SULFATE; WATER

Ciclopirox Gel 0.77%

FOR DERMATOLOGIC USE ONLY.

NOT FOR USE IN EYES.

Rx Only

DESCRIPTION

Ciclopirox gel 0.77% contains a synthetic antifungal agent, ciclopirox USP. It is intended for topical dermatologic use only.

Each gram of ciclopirox gel contains 7.70 mg of ciclopirox USP in a gel consisting of carbomer 940, isopropyl alcohol, and medium chain triglycerides, sodium hydroxide, sodium lauryl sulfate, and purified water.

Ciclopirox gel is a white, slightly fluid gel.

The chemical name for ciclopirox USP is 6-cyclohexyl-1-hydroxy-4-methyl-2(1H)-pyridinone, with the empirical formula C12H17NO2 and a molecular weight of 207.27. The CAS Registry Number is [29342-05-0]. The chemical structure is:

CLINICAL PHARMACOLOGY

Mechanism of Action

Ciclopirox is a hydroxypyridone antifungal agent although the relevance of this property for the indication of seborrheic dermatitis is not known. Ciclopirox acts by chelation of polyvalent cations (Fe^3+ or Al^3+), resulting in the inhibition of the metal-dependent enzymes that are responsible for the degradation of peroxides within the fungal cell.

Pharmacokinetics

A comparative study of the pharmacokinetics of ciclopirox gel and ciclopirox cream (ciclopirox olamine) 0.77% in 18 healthy males indicated that systemic absorption of ciclopirox from ciclopirox gel was higher than that of ciclopirox cream. A 5 gm dose of ciclopirox gel produced a mean (±SD) peak serum concentration of 25.02 (±20.6) ng/mL total ciclopirox and 5 gm of ciclopirox cream produced 18.62 (±13.56) ng/mL total ciclopirox. Approximately 3% of the applied ciclopirox was excreted in the urine within 48 hours after application, with a renal elimination half-life of about 5.5 hours.

In a study of ciclopirox gel, 16 men with moderate to severe tinea cruris applied approximately 15 grams/day of the gel for 14.5 days. The mean (±SD) dose-normalized values of Cmax for total ciclopirox in serum were 100 (±42) ng/mL on Day 1 and 238 (±144) ng/mL on Day 15. During the 10 hours after dosing on Day 1, approximately 10% of the administered dose was excreted in the urine.

Microbiology

Ciclopirox is a hydroxypyridinone antifungal agent that inhibits the growth of pathogenic dermatophytes. Ciclopirox has been shown to be active against most strains of the following microorganisms both in vitro and in clinical infections as described in the INDICATIONS AND USAGE section:

Trichophyton rubrum, Trichophyton mentagrophytes, and Epidermophyton floccosum

INDICATIONS AND USAGE

Superficial Dermatophyte Infections

Ciclopirox gel is indicated for the topical treatment of interdigital tinea pedis and tinea corporis due to Trichophyton rubrum, Trichophyton mentagrophytes, or Epidermophyton floccosum.

Seborrheic Dermatitis

Ciclopirox gel is indicated for the topical treatment of seborrheic dermatitis of the scalp.

CONTRAINDICATIONS

Ciclopirox gel is contraindicated in individuals who have shown hypersensitivity to any of its components.

WARNINGS

Ciclopirox gel is not for ophthalmic, oral, or intravaginal use.

Keep out of reach of children.

PRECAUTIONS

If a reaction suggesting sensitivity or chemical irritation should occur with the use of ciclopirox gel, treatment should be discontinued and appropriate therapy instituted. A transient burning sensation may occur, especially after application to sensitive areas. Avoid contact with eyes. Efficacy of ciclopirox gel in immunosuppressed individuals has not been studied. Seborrheic dermatitis in association with acne, atopic dermatitis, Parkinsonism, psoriasis and rosacea has not been studied with ciclopirox gel. Efficacy in the treatment of plantar and vesicular types of tinea pedis has not been established.

Information for Patients

The patient should be told the following:

1. Use ciclopirox gel as directed by the physician. Avoid contact with the eyes and mucous membranes. Ciclopirox gel is for external use only.
2. Use the medication for fungal infections for the full treatment time even though symptoms may have improved, and notify the physician if there is no improvement after 4 weeks.
3. A transient burning/stinging sensation may be felt. This may occur in approximately 15% to 20% of cases, when ciclopirox gel is used to treat seborrheic dermatitis of the scalp.
4. Inform the physician if the area of application shows signs of increased irritation or possible sensitization (redness with itching, burning, blistering, swelling, and/or oozing).
5. Avoid the use of occlusive dressings.
6. Do not use this medication for any disorder other than that for which it is prescribed.

Carcinogenesis, Mutagenesis, Impairment of Fertility

A 104-week dermal carcinogenicity study in mice was conducted with ciclopirox cream formulation applied at doses up to 1.93% (100 mg/kg/day or 300 mg/m^2/day). No increase in drug related neopalsms was noted when compared to control.

The following in vitro genotoxicity tests have been conducted with ciclopirox: evaluation of gene mutation in the Ames Salmonella and E. coli assays (negative); chromosome aberration assays in V79 Chinese hamster lung fibroblast cells, with and without metabolic activation (positive); chromosome aberration assays in V79 Chinese hamster lung fibroblast cells in the presence of supplemental Fe^3+, with and without metabolic activation (negative); gene mutation assays in the HGPRT-test with V79 Chinese hamster lung fibroblast cells (negative); and a primary DNA damage assay (i.e., unscheduled DNA synthesis assay in A549 human cells) (negative). An in vitro cell transformation assay in BALB/c 3T3 cells was negative for cell transformation. In an in vivo Chinese hamster bone marrow cytogenetic assay, ciclopirox was negative for chromosome aberrations at a dosage of 5,000 mg/kg body weight.

A combined oral fertility and embryofetal developmental study was conducted in rats with ciclopirox olamine. No effect on fertility or reproductive performance was noted at the highest dose tested of 3.85 mg/kg/day ciclopirox (approximately 1.2 times the maximum recommended human dose based on body surface area comparisons).

Pregnancy

Teratogenic effects: Pregnancy Category B

There are no adequate or well-controlled studies in pregnant women. Therefore, ciclopirox gel should be used during pregnancy only if the potential benefit justifies the potential risk to the fetus.

Oral embryofetal developmental studies were conducted in mice, rats, rabbits and monkeys. Ciclopirox or ciclopirox olamine was orally administered during the period of organogenesis. No maternal toxicity, embryotoxicity or teratogenicity were noted at the highest doses of 77, 125, 80 and 38.5 mg/kg/day ciclopirox in mice, rats, rabbits and monkeys, respectively (approximately 11, 37, 51 and 24 times the maximum recommended human dose based on body surface area comparisons, respectively).

Dermal embryofetal developmental studies were conducted in rats and rabbits with ciclopirox olamine dissolved in PEG 400. Ciclopirox olamine was topically administered during the period of organogenesis. No maternal toxicity, embryotoxicity or teratogenicity were noted at the highest doses of 92 mg/kg/day and 77 mg/kg/day ciclopirox in rats and rabbits, respectively (approximately 27 and 49 times the maximum recommended human dose based on body surface area comparisons, respectively).

Nursing Mothers

It is not known whether this drug is excreted in human milk. Since many drugs are excreted in human milk, caution should be exercised when ciclopirox gel is administered to a nursing woman.

Pediatric Use

The efficacy and safety of ciclopirox gel in pediatric patients below the age of 16 years have not been established.

ADVERSE REACTIONS

In clinical trials, 140 (39%) of 359 subjects treated with ciclopirox gel reported adverse experiences, irrespective of relationship to test materials, which resulted in 8 subjects discontinuing treatment. The most frequent experience reported was skin burning sensation upon application, which occurred in approximately 34% of seborrheic dermatitis patients and 7% of tinea pedis patients. Adverse experiences occurring between 1% to 5% were contact dermatitis and pruritus. Other reactions that occurred in less than 1% included dry skin, acne, rash, alopecia, pain upon application, eye pain, and facial edema.

DOSAGE AND ADMINISTRATION

Superficial Dermatophyte Infections

Gently massage ciclopirox gel into the affected areas and surrounding skin twice daily, in the morning and evening immediately after cleaning or washing the areas to be treated. Interdigital tinea pedis and tinea corporis should be treated for 4 weeks. If a patient shows no clinical improvement after 4 weeks of treatment, the diagnosis should be reviewed.

Seborrheic Dermatitis of the Scalp

Apply ciclopirox gel to affected scalp areas twice daily, in the morning and evening for 4 weeks. Clinical improvement usually occurs within the first week with continuing resolution of signs and symptoms through the fourth week of treatment. If a patient shows no clinical improvement after 4 weeks of treatment, the diagnosis should be reviewed.

HOW SUPPLIED

Ciclopirox gel 0.77% is supplied in aluminum tubes and LDPE tubes.

30 g tubes (NDC 68462-455-35), 45 g tubes (NDC 68462-455-47) and 100 g tubes (NDC 68462-455-94).

Store at 20°C to 25°C (68°F to 77°F) [See USP Controlled Room Temperature].

Distributed by:

Glenmark Pharmaceuticals Inc., USA

Elmwood Park, NJ 07407

Questions? 1 (888)721-7115

www.glenmarkpharma-us.com

April 2025